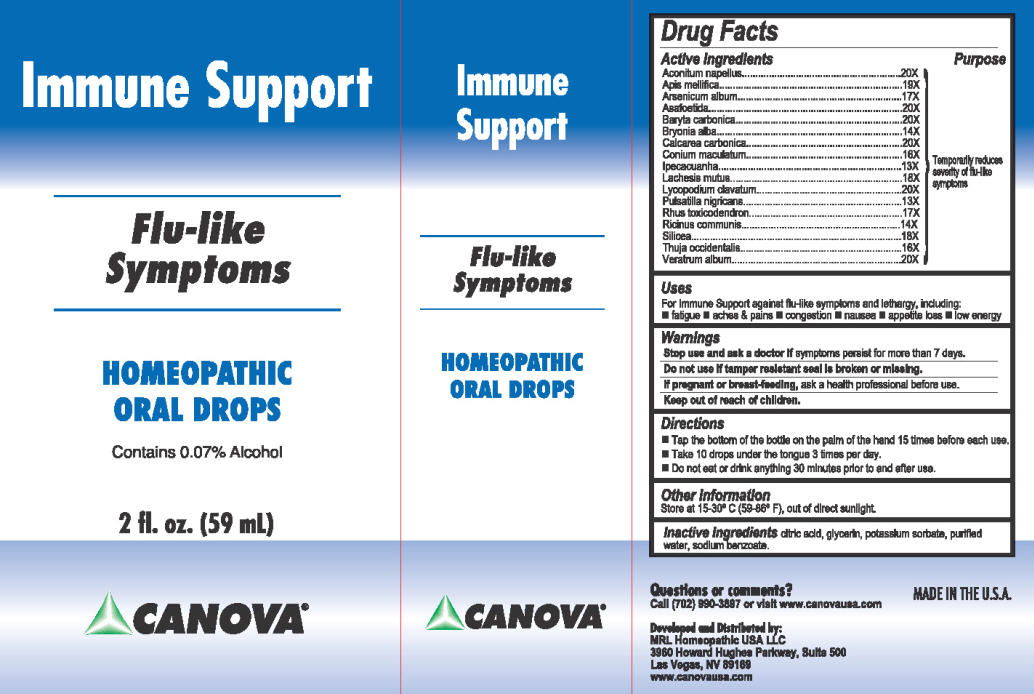 DRUG LABEL: Canova Immune Support
NDC: 58088-001 | Form: LIQUID
Manufacturer: MRL Homeopathic USA LLC
Category: homeopathic | Type: HUMAN OTC DRUG LABEL
Date: 20130508

ACTIVE INGREDIENTS: ACONITUM NAPELLUS 20 [hp_X]/59 mL; APIS MELLIFERA 19 [hp_X]/59 mL; ARSENIC TRIOXIDE 17 [hp_X]/59 mL; ASAFETIDA 20 [hp_X]/59 mL; BARIUM CARBONATE 20 [hp_X]/59 mL; BRYONIA ALBA ROOT 14 [hp_X]/59 mL; OYSTER SHELL CALCIUM CARBONATE, CRUDE 20 [hp_X]/59 mL; CONIUM MACULATUM FLOWERING TOP 16 [hp_X]/59 mL; IPECAC 13 [hp_X]/59 mL; LACHESIS MUTA VENOM 18 [hp_X]/59 mL; LYCOPODIUM CLAVATUM SPORE 20 [hp_X]/59 mL; PULSATILLA VULGARIS 13 [hp_X]/59 mL; TOXICODENDRON PUBESCENS LEAF 17 [hp_X]/59 mL; CASTOR OIL 14 [hp_X]/59 mL; SILICON DIOXIDE 18 [hp_X]/59 mL; THUJA OCCIDENTALIS ROOT 16 [hp_X]/59 mL; VERATRUM ALBUM ROOT 20 [hp_X]/59 mL
INACTIVE INGREDIENTS: CITRIC ACID MONOHYDRATE; GLYCERIN; POTASSIUM SORBATE; WATER; SODIUM BENZOATE

CANOVA® Immune Support

Active ingredient

Aconitum napellus..............20X

Apis mellifica......................19X

Arsenicum album................17X

Asafoetida...........................20X

Baryta carbonica.................20X

Bryonia alba........................14X

Calcarea carbonica..............20X

Conium maculatum.............16X

Ipecacuanha.........................13X

Lachesis mutus....................18X

Lycopodium clavatum.........20X

Pulsatilla nigricans...............13X

Rhus toxicodendron.............17X

Ricinus communis...............14X

Silicea..................................18X

Thuja occidentalis................16X

Veratrum album...................20X

Purpose

Temporarily reduces severity of flu-like symptoms

Uses

For Immune Support against flu-like symptoms and lethargy, including:

- fatigue
- aches & pains
- congestion
- nausea
- appetite loss
- low energy

Warnings

Stop use and ask a doctor if symptoms persist for more than 7 days.
Do not use if tamper resistant seal is broken or missing.
If pregnant or breast-feeding, ask a health professional before use.

Directions

- Tap the bottom of the bottle on the palm of the hand 15 times before each use.
- Take 10 drops under the tongue 3 times per day.
- Do not eat or drink anything 30 minutes prior to and after use.

Other Information

Store at 15-30° C (59-86° F), out of direct sunlight.

Inactive ingredients

citric acid, glycerin, potassium sorbate, purified water, sodium benzoate.

Questions or comments?

Call (702) 990-3897 or visit www.canovausa.com

Developed and Distributed by:
MRL Homeopathic USA LLC
3960 Howard Hughes Parkway, Suite 500
Las Vegas, NV 89189
www.canovausa.com

MADE IN THE U.S.A.

Patient Information

When was Canova Immune Support developed?

In the 1960s, Dr. Francisco Canova, an Argentinean medical doctor and trained homeopath, developed a homeopathic medicine, later called Canova Immune Support, for the debilitating effects of a compromised immune system. Canova Immune Support developed a loyal following reaching over 10,000 users by the early 1990s.

What is Canova Immune Support?

Canova Immune Support is a homeopathic medicine made from 17 different plants, mineral and animal ingredients. It provides favorable support to your immune system in your day-to-day activities by boosting the body's immune system and enhancing resistance to immune challenges due to fatigue, exposure to environmental challenges, and stress. Canova Immune Support is a complement, not replacement, to traditional (allopathic) medicine.

Can Canova Immune Support be used to treat recurring illnesses?

For patients with recurring illnesses, Canova Immune Support aims to reduce the intensity and frequency of episodes or outbreaks, as with allergies or herpes, for example.*

What is the main benefit of taking Canova Immune Support?

Canova Immune Support stimulates the human body’s defenses against infection, disease, or other unwanted biological invasion, providing relief for symptoms experienced by people with a weakened immune system, such as fatigue, nausea, appetite loss, and aches and pains. The ultimate and main benefit of Canova Immune Support is the improved quality of life for people fighting incapacitating symptoms, such as the severity of those associated with the flu.*

Can Canova Immune Support be taken in conjunction with other medications?

The extremely small doses of each active homeopathic ingredient of Canova Immune Support assure it is safe and has no known side effects or contraindications. Canova Immune Support can be safely taken with other conventional medicines and is usually recommended as a complement to other treatments.*

Can I give Canova Immune Support to my children?

Homeopathic medicines are generally safe for children. Please see package labeling for specific drug facts and dosage recommendations. For a child under the age specified on the label, please check with a doctor or pharmacist first.

Can I use Canova Immune Support by myself, without a doctor's supervision?

Canova Immune Support may be used for self-diagnosable conditions that do not require a doctor’s supervision. Canova Immune Support is clearly labeled with warnings and directions for use, as per FDA Regulations. Always read and follow label directions when taking Canova without a doctor’s supervision.

Is Canova Immune Support safe to use when pregnant?

As with any medicine, pregnant women should seek the advice of a medical professional before use.

How popular is Canova Immune Support?

Canova Immune Support is currently used by an estimated 30,000 people worldwide.

Has Canova Immune Support been researched?

Several Universities and Research Institutions conducted various research studies on Canova Immune Support and published their results in 16 international life science journals, seven university published papers, and 19 international congress papers.

What is the best way to store Canova Immune Support?

The best way to store Canova Immune Support is away from direct sunlight, TV sets, radios, microwave ovens, cell phones, other electrical appliances and fragrant substances, such as perfumes. It is also important that the bottle be tightly closed after each use.

*This statement has not been approved by the FDA. This product is not intended to treat, cure or prevent any disease.

Questions or comments?
Call (702) 990-3897 or visit www.canovausa.com

Developed and Distributed by:
MRL Homeopathic USA LLC
3960 Howard Hughes Parkway, Suite 500
Las Vegas, NV 89169 www.canovausa.com

MADE IN THE U.S.A.

Package/Label Principal Display Panel

Carton Label